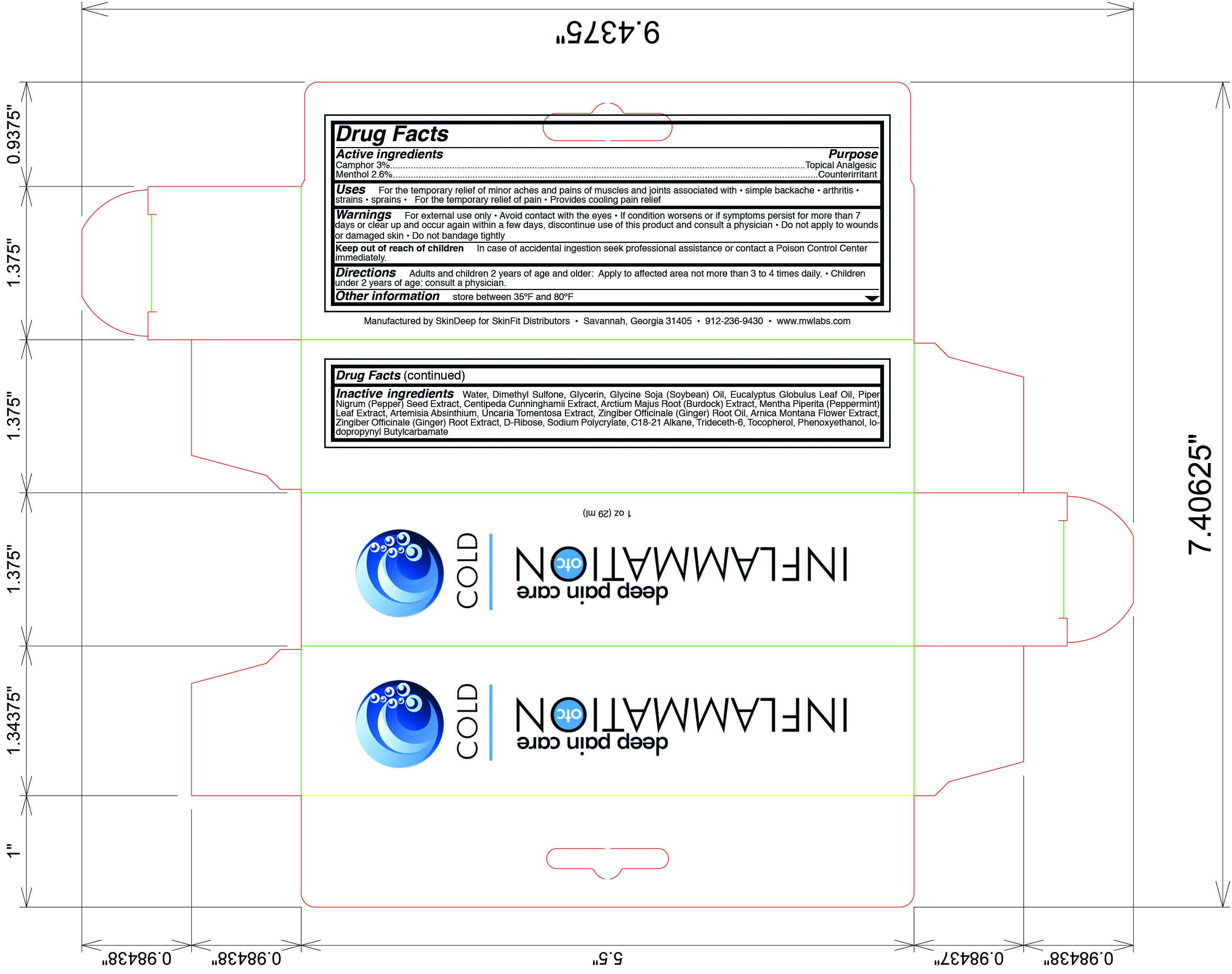 DRUG LABEL: Inflammation OTC
NDC: 45156-5610 | Form: LOTION
Manufacturer: Skin Deep
Category: otc | Type: HUMAN OTC DRUG LABEL
Date: 20110816

ACTIVE INGREDIENTS: Camphor (Natural) 18 g/600 g; Menthol 16 g/600 g
INACTIVE INGREDIENTS: Water; Glycerin; Dimethyl Sulfone; Black Pepper Oil; Soybean Oil; Arctium Lappa Root; Peppermint; Wormwood; Cat's Claw; Ginger Oil; Arnica Montana; Ginger; Trideceth-6; Alpha-Tocopherol; Phenoxyethanol; Iodopropynyl Butylcarbamate

Drug Facts

Active Ingredient

Camphor (3.0%)

Menthol (2.6%)

Purpose

Topical Analgesic

Counterirritant

Uses

For temporary relief of minor aches and pains of muscles and joints associated with

- simple backache
- arthritis
- strains
- sprains

Warnings

For external use only

Avoid contact with the eyes

If condition worsens, or if symptoms persist for more than 7 days or clear up and occur again within a few days, discontinue use of this product and consult a physician

Do not apply to wounds or damaged skin

Do not bandage tightly

Keep out of reach of children

In case of accidental ingestion seek professional assistance or contact a poison control immediately

Directions

Adults and children 2 years of age and older- Apply to affected area not more than 3 to 4 times daily.

Children under 2 years of age- Consult a physician.

Inactive Ingredients

water, dimethyl sulfone, glycerin, glycine soja (soybean) oil, eucalyptus globulus oil, piper nigrum (pepper) seed extract, centipedia cunninghamii extract, arctium majus root (burdock) extract, mentha piperita (peppermint) leaf extract, artemisia absinthium, uncaria tomentosa extract, zingiber officinale (ginger) root oil, arnica montana flower extract, zingiber officinale (ginger) root extract, d-ribose, sodium polycrylate, c18-21 alkane, trideceth-6, tocopherol, phenoxyethanol, iodopropynyl butylcarbamate

Questions or Comments

Store between 35 F and 80 F

call 1-912-236-9430 weekdays

Principal Display Panel

Inflammation OTC

Deep Pain Care Cold

New wt 1.1 oz. (31 mL)

Manufactured by SkinDeep for SkinFit Distributors

Savannah, GA 31405

Tel: 912-236-9430
www.mwlabs.com